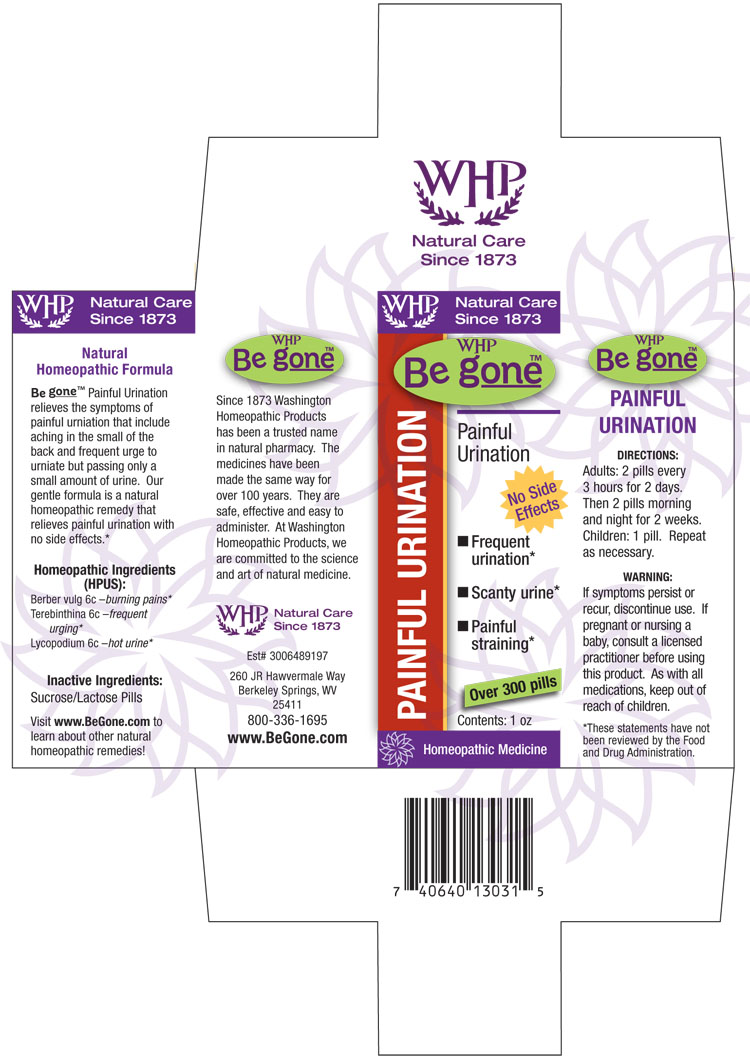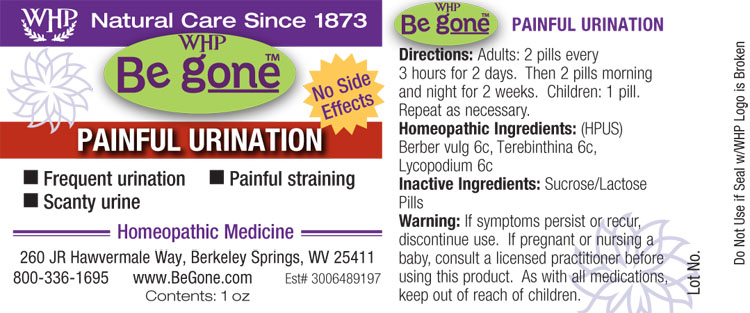 DRUG LABEL: WHP Be gone Painful Urination
NDC: 68428-748 | Form: PELLET
Manufacturer: Washington Homeopathic Products
Category: homeopathic | Type: HUMAN OTC DRUG LABEL
Date: 20140508

ACTIVE INGREDIENTS: BERBERIS VULGARIS ROOT BARK 6 [hp_C]/1 1; TURPENTINE OIL 6 [hp_C]/1 1; LYCOPODIUM CLAVATUM SPORE 6 [hp_C]/1 1
INACTIVE INGREDIENTS: SUCROSE; LACTOSE

DRUG FACTS

ACTIVE INGREDIENTS

BERBER VULG

TEREBINTHINA

LYCOPODIUM

USES

Relieves the symptoms of painful urination that include aching in the small of the back and frequent urge to urinate but passing only a small amount of urine.

KEEP OUT OF REACH OF CHILDREN

As with all medications, keep out of reach of children.

INDICATIONS

BERBER VULG Burning pains

TEREBINTHINA Frequent urging

LYCOPODIUM Hot urine

STOP USE AND ASK DOCTOR

If symptoms persist or recur, discontinue use. If pregnant or nursing a baby, consult a licensed practitioner before using this product.

DIRECTIONS

Adults: 2 pills every 3 hours for 2 days. Then 2 pills morning and night for 2 weeks.

Children: 1 pill.

Repeat as necessary.

INACTIVE INGREDIENTS

Sucrose/Lactose